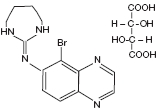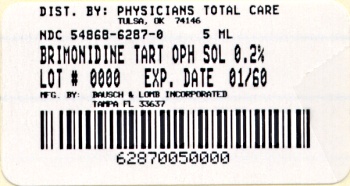 DRUG LABEL: Brimonidine Tartrate
NDC: 54868-6287 | Form: SOLUTION/ DROPS
Manufacturer: Physicians Total Care, Inc.
Category: prescription | Type: HUMAN PRESCRIPTION DRUG LABEL
Date: 20130219

ACTIVE INGREDIENTS: BRIMONIDINE TARTRATE 2 mg/1 mL
INACTIVE INGREDIENTS: BENZALKONIUM CHLORIDE; CITRIC ACID MONOHYDRATE; HYDROCHLORIC ACID; POLYVINYL ALCOHOL; WATER; SODIUM CHLORIDE; SODIUM CITRATE; SODIUM HYDROXIDE

Brimonidine Tartrate
Ophthalmic Solution 0.2% (Sterile)

Rx only

DESCRIPTION:

Brimonidine Tartrate Ophthalmic Solution 0.2% is a relatively selective alpha-2 adrenergic agonist for ophthalmic use. In solution, brimonidine tartrate ophthalmic solution 0.2% has a clear, greenish-yellow color. It has an osmolality of 280-330 mOsml/kg and a pH of 5.6-6.6 The structural formula is

C11H10BrN5 • C4H6O6

Mol. Wt. 442.24 (as the tartrate salt)

Chemical Name: 5-bromo-6-(2-imidazolidinylideneamino) quinoxaline L-tartrate.

CAS Number 59803-98-4

Each mL Contains:

ACTIVE: Brimonidine tartrate: 0.2% (2 mg/mL).

INACTIVES: Citric Acid, Polyvinyl Alcohol, Sodium Chloride, Sodium Citrate, Purified Water. Hydrochloric Acid and/or Sodium Hydroxide may be added to adjust pH.

PRESERVATIVE ADDED: Benzalkonium Chloride (0.05 mg).

CLINICAL PHARMACOLOGY:

Mechanism of Action:

Brimonidine tartrate ophthalmic solution 0.2% is an alpha adrenergic receptor agonist. It has a peak ocular hypotensive effect occurring at two hours post-dosing. Fluorophotometric studies in animals and humans suggest that brimonidine tartrate has a dual mechanism of action by reducing aqueous humor production and increasing uveoscleral outflow.

Pharmacokinetics:

After ocular administration of a 0.2% solution, plasma concentrations peaked within 1 to 4 hours and declined with a systemic half-life of approximately 3 hours. In humans, systemic metabolism of brimonidine is extensive. It is metabolized primarily by the liver. Urinary excretion is the major route of elimination of the drug and its metabolites. Approximately 87% of an orally administered radioactive dose was eliminated within 120 hours, with 74% found in the urine.

Clinical Evaluations:

Elevated IOP presents a major risk factor in glaucomatous field loss. The higher the level of lOP, the greater the likelihood of optic nerve damage and visual field loss. Brimonidine tartrate has the action of lowering intraocular pressure with minimal effect on cardiovascular and pulmonary parameters.

In comparative clinical studies with timolol 0.5%, lasting up to one year, the lOP lowering effect of brimonidine tartrate ophthalmic solution 0.2% was approximately 4-6 mmHg compared with approximately 6 mmHg for timolol. In these studies, both patient groups were dosed BID; however, due to the duration of action of brimonidine tartrate ophthalmic solution 0.2%, it is recommended that brimonidine tartrate ophthalmic solution 0.2% be dosed TID. Eight percent of subjects were discontinued from studies due to inadequately controlled intraocular pressure, which in 30% of these patients occurred during the first month of therapy. Approximately 20% were discontinued due to adverse experiences.

INDICATIONS AND USAGE:

Brimonidine tartrate ophthalmic solution 0.2% is indicated for lowering intraocular pressure in patients with open-angle glaucoma or ocular hypertension. The lOP lowering efficacy of brimonidine tartrate ophthalmic solution 0.2% diminishes over time in some patients. This loss of effect appears with a variable time of onset in each patient and should be closely monitored.

CONTRAINDICATIONS:

Brimonidine tartrate ophthalmic solution 0.2% is contraindicated in patients with hypersensitivity to brimonidine tartrate or any component of this medication. It is also contraindicated in patients receiving monoamine oxidase (MAO) inhibitor therapy.

PRECAUTIONS:

General:

Although brimonidine tartrate ophthalmic solution 0.2% had minimal effect on blood pressure of patients in clinical studies, caution should be exercised in treating patients with severe cardiovascular disease.

Brimonidine tartrate ophthalmic solution 0.2% has not been studied in patients with hepatic or renal impairment; caution should be used in treating such patients.

Brimonidine tartrate ophthalmic solution 0.2% should be used with caution in patients with depression, cerebral or coronary insufficiency, Raynaud’s phenomenon, orthostatic hypotension or thromboangiitis obliterans.

During the studies there was a loss of effect in some patients. The IOP-lowering efficacy observed with brimonidine tartrate ophthalmic solution 0.2% during the first month of therapy may not always reflect the long-term level of IOP reduction. Patients prescribed IOP-lowering medication should be routinely monitored for IOP.

Information for Patients:

The preservative in brimonidine tartrate ophthalmic solution 0.2%, benzalkonium chloride, may be absorbed by soft contact lenses. Patients wearing soft contact lenses should be instructed to wait at least 15 minutes after instilling brimonidine tartrate ophthalmic solution 0.2% to insert soft contact lenses.

As with other drugs in this class, brimonidine tartrate ophthalmic solution 0.2% may cause fatigue and/or drowsiness in some patients. Patients who engage in hazardous activities should be cautioned of the potential for a decrease in mental alertness.

Drug Interactions:

Although specific drug interaction studies have not been conducted with brimonidine tartrate ophthalmic solution 0.2%, the possibility of an additive or potentiating effect with CNS depressants (alcohol, barbiturates, opiates, sedatives, or anesthetics) should be considered. Alpha-agonists, as a class, may reduce pulse and blood pressure. Caution in using concomitant drugs such as beta-blockers (ophthalmic and systemic), antihypertensives and/or cardiac glycosides is advised.

Tricyclic antidepressants have been reported to blunt the hypotensive effect of systemic clonidine. It is not known whether the concurrent use of these agents with brimonidine tartrate ophthalmic solution 0.2% in humans can lead to resulting interference with the IOP lowering effect. No data on the level of circulating catecholamines after brimonidine tartrate ophthalmic solution 0.2% are available. Caution, however, is advised in patients taking tricyclic antidepressants which can affect the metabolism and uptake of circulating amines.

Carcinogenesis, mutagenesis, impairment of fertility:

No compound-related carcinogenic effects were observed in either mice or rats following a 21-month and 24-month study, respectively. In these studies, dietary administration of brimonidine tartrate at doses up to 2.5 mg/kg/day in mice and 1.0 mg/kg/day in rats achieved ~77 and 118 times, respectively, the plasma drug concentration estimated in humans treated with one drop brimonidine tartrate ophthalmic solution 0.2% into both eyes 3 times per day.

Brimonidine tartrate was not mutagenic or cytogenic in a series of in vitro and in vivo studies including the Ames test, chromosomal aberation assay in Chinese Hamster Ovary (CHO) cells, a host-mediated assay and cytogenic studies in mice, and dominant lethal assay.

Reproductive studies performed in rats with oral doses of 0.66 mg base/kg revealed no evidence of harm to the fetus due to brimonidine tartrate ophthalmic solution 0.2%.

Pregnancy: Teratogenic Effects: Pregnancy Category B.

Reproductive studies performed in rats with oral doses of 0.66 mg base/kg revealed no evidence of harm to the fetus due to brimonidine tartrate ophthalmic solution 0.2%. Dosing at this level produced 100 times the plasma drug concentration level seen in humans following multiple ophthalmic doses.

There are no adequate and well-controlled studies in pregnant women. In animal studies, brimonidine crossed the placenta and entered into the fetal circulation to a limited extent. Brimonidine tartrate ophthalmic solution 0.2% should be used during pregnancy only if the potential benefit to the mother justifies the potential risk to the fetus.

Nursing Mothers:

It is not known whether this drug is excreted in human milk; in animal studies brimonidine tartrate was excreted in breast milk. A decision should be made whether to discontinue nursing or to discontinue the drug, taking into account the importance of the drug to the mother.

Pediatric Use:

In a well-controlled clinical study conducted in pediatric glaucoma patients (ages 2 to 7 years) the most commonly observed adverse events with brimonidine tartrate ophthalmic solution 0.2% dosed three times daily were somnolence (50% - 83% in patients ages 2 to 6 years) and decreased alertness. In pediatric patients 7 years of age or older (>20kg), somnolence appears to occur less frequently (25%). The most commonly observed adverse event was somnolence. Approximately 16% of patients on brimonidine tartrate ophthalmic solution discontinued from the study due to somnolence.

The safety and effectiveness of brimonidine tartrate ophthalmic solution 0.2% have not been studied in pediatric patients below the age of 2 years. Brimonidine tartrate ophthalmic solution 0.2% is not recommended for use in pediatric patients under the age of 2 years. (Also refer to Adverse Reactions section).

Geriatric Use:

No overall differences in safety or effectiveness have been observed between elderly and other adult patients.

ADVERSE REACTIONS:

Adverse events occurring in approximately 10-30% of the subjects, in descending order of incidence, included oral dryness, ocular hyperemia, burning and stinging, headache, blurring, foreign body sensation, fatigue/drowsiness, conjunctival follicles, ocular allergic reactions, and ocular pruritus.

Events occurring in approximately 3-9% of the subjects, in descending order included corneal staining/erosion, photophobia, eyelid erythema, ocular ache/pain, ocular dryness, tearing, upper respiratory symptoms, eyelid edema, conjunctival edema, dizziness, blepharitis, ocular irritation, gastrointestinal symptoms, asthenia, conjunctival blanching, abnormal vision and muscular pain.

The following adverse reactions were reported in less than 3% of the patients: lid crusting, conjunctival hemorrhage, abnormal taste, insomnia, conjunctival discharge, depression, hypertension, anxiety, palpitations/arrhythmias, nasal dryness and syncope.

The following events have been identified during post-marketing use of brimonidine tartrate ophthalmic solution 0.2% in clinical practice. Because they are reported voluntarily from a population of unknown size, estimates of frequency cannot be made. The events, which have been chosen for inclusion due to either their seriousness, frequency of reporting, possible causal connection to brimonidine tartrate ophthalmic solution 0.2%, or a combination of these factors, include: bradycardia; hypotension; iritis; miosis; skin reactions (including erythema, eyelid pruritis, rash, and vasodilation); and tachycardia. Apnea, bradycardia, hypotension, hypothermia, hypotonia, and somnolence have been reported in infants receiving brimonidine tartrate ophthalmic solution 0.2%.

OVERDOSAGE:

No information is available on overdosage in humans. Treatment of an oral overdose includes supportive and symptomatic therapy; a patent airway should be maintained.

DOSAGE AND ADMINISTRATION:

The recommended dose is one drop of brimonidine tartrate ophthalmic solution 0.2% in the affected eye(s) three times daily, approximately 8 hours apart.

Brimonidine tartrate ophthalmic solution 0.2% may be used concomitantly with other topical ophthalmic drug products to lower intraocular pressure. If more than one topical ophthalmic product is being used, the products should be administered at least 5 minutes apart.

HOW SUPPLIED:

Brimonidine Tartrate Ophthalmic Solution 0.2% is supplied sterile in a plastic bottle with a controlled drop tip in the following sizes:

5 mL bottles NDC 54868-6287-0

10 mL bottles NDC 54868-6287-1

STORAGE AND HANDLING

Storage: Store between 15° – 25°C (59° – 77°F).

KEEP OUT OF THE REACH OF CHILDREN.

DO NOT USE IF IMPRINTED “Protective Seal” WITH YELLOW (mortar and pestle symbol) IS NOT INTACT.

Revised July 2008

Bausch & Lomb Incorporated
Tampa, FL 33637

©Bausch & Lomb Incorporated

9104701 (Folded) 9104601 (Flat)
Prod. No. 411

Additional barcode labeling by:
Physicians Total Care, Inc.
Tulsa, OK 74146

PACKAGE/LABEL PRINCIPAL DISPLAY PANEL:

NDC 54868-6287-0

5 mL

Brimonidine Tartrate Ophthalmic Solution 0.2% (Sterile)

Rx only